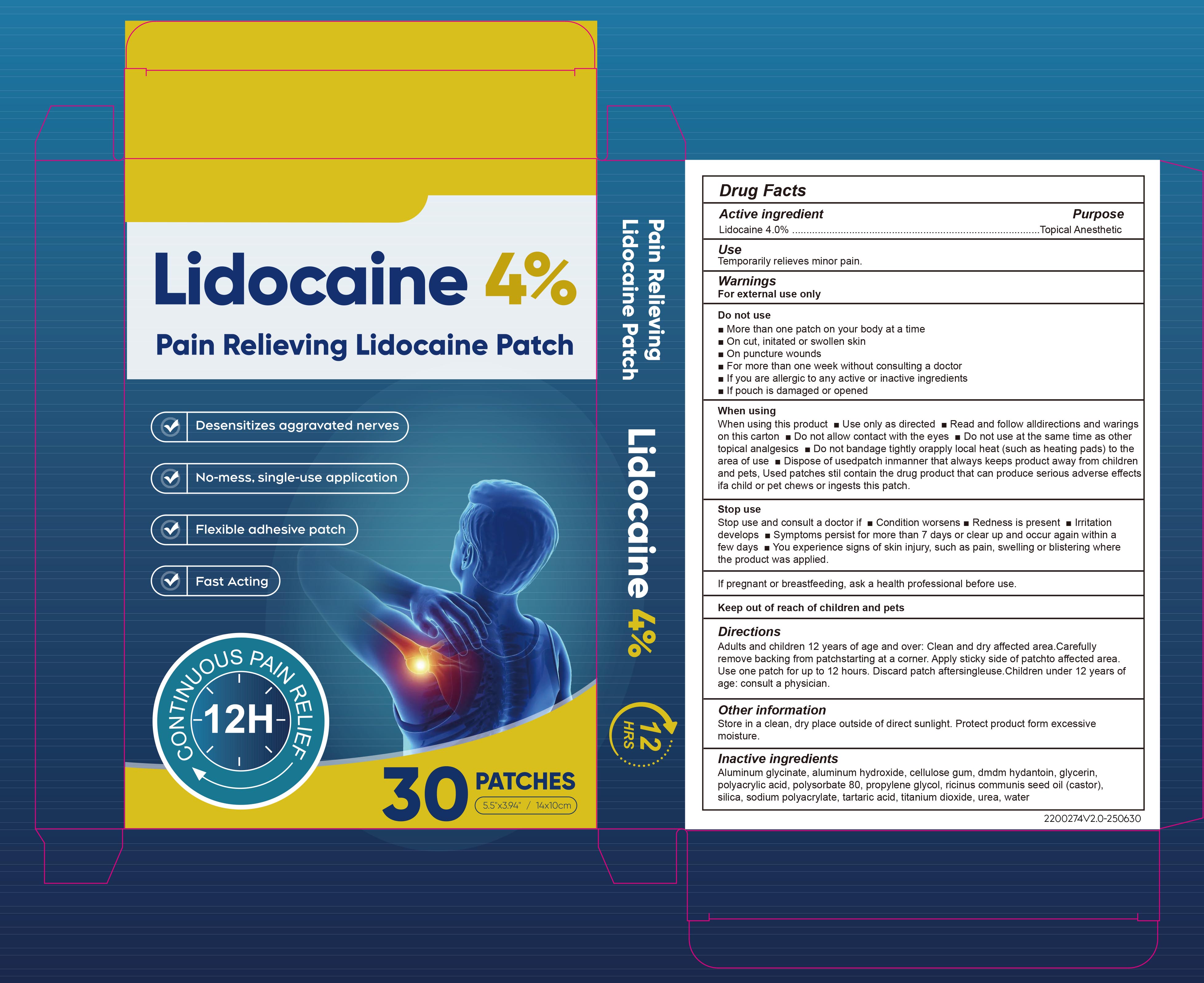 DRUG LABEL: Lidocaine Patch
NDC: 85839-008 | Form: PATCH
Manufacturer: Shenzhen Finona Information Technology Co., Ltd
Category: otc | Type: HUMAN OTC DRUG LABEL
Date: 20251203

ACTIVE INGREDIENTS: LIDOCAINE 0.04 g/1 1
INACTIVE INGREDIENTS: ALUMINUM GLYCINATE; ALUMINUM HYDROXIDE; CELLULOSE GUM; DMDM HYDANTOIN; GLYCERIN; PROPYLENE GLYCOL; SILICA; SODIUM POLYACRYLATE (2500000 MW); TARTARIC ACID; TITANIUM DIOXIDE; POLYSORBATE 80; POLYACRYLIC ACID (250000 MW); RICINUS COMMUNIS (CASTOR) SEED OIL; WATER; UREA

85839-008 Lidocaine Patch

ACTIVE INGREDIENT

Lidocaine 4%

PURPOSE

Topical Anesthetic

INDICATIONS AND USAGE

Temporarily relieves minor pain

WARNINGS

For external use only

DO NOT USE

More than one patch on your body at a time On cut, initated or swollen skin Onpuncture wounds. For more than one week without consulting a doctor lf you are allergicto any active or inactive ingredients lf pouch is damaged or opened.

When using this product Use only as directed Read and follow alldirections and waringson this carton Do not allow contact with the eyes. Do not use at the same time as othertopical analgesics Do not bandage tightly orapply local heat (such as heating pads) to thearea of use Dispose of usedpatch inmanner that always keeps product away from childrenand pets, Used patches stil contain the drug product that can produce serious adverse effectsifa child or pet chews or ingests this patch.

Stop use and consult a doctor if, Condition worsens,Redness is present lrritationdevelops Symptoms persist for more than 7 days or clear up and occur again within afew days You experience signs of skin injury, such as pain, swelling or blistering wherethe product was applied.

Keep out of reach of children and pets

DOSAGE AND ADMINISTRATION

Adults and children 12 years of age and over: Clean and dry affected area.Carefully remove backing from patchstarting at a corner. Apply sticky side of patchto affected area.Use one patch for up to 12 hours. Discard patch aftersingleuse.
Children under 12 years of age: consult a physician.

INACTIVE INGREDIENT

Aluminum Glycinate
Aluminum Hydroxide
Cellulose Gum
DMDM hydantoin
Glycerin
Polyacrylic Acid
Polysorbate 80
Propylene Glycol
Ricinus Communis Seed Oil (castor)
Silica
Sodium Polyacrylate
Tartaric Acid
Titanium Dioxide
Urea
Water